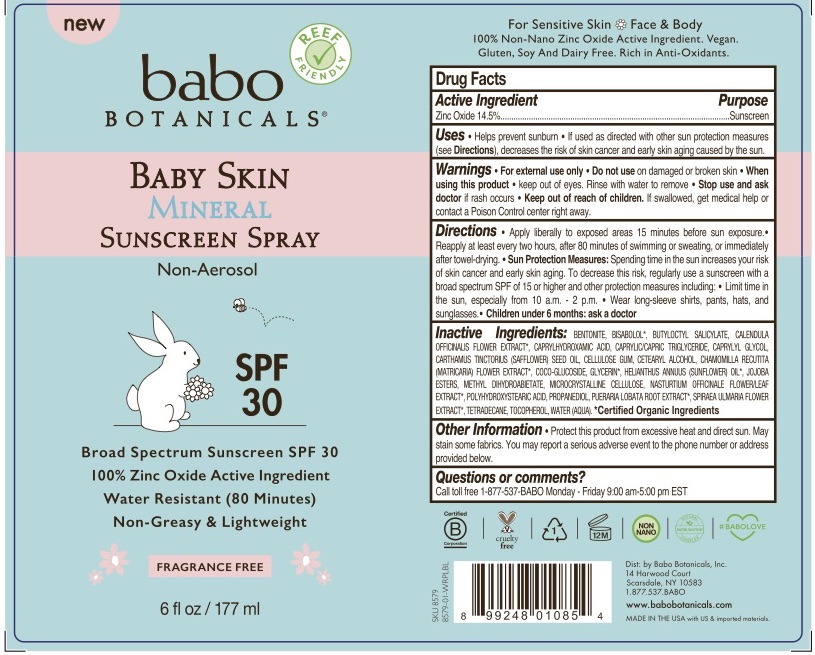 DRUG LABEL: Babo Baby Skin Mineral Sunscreen FF
NDC: 79265-8579 | Form: SPRAY
Manufacturer: Babo Botanicals, Inc.
Category: otc | Type: HUMAN OTC DRUG LABEL
Date: 20241212

ACTIVE INGREDIENTS: ZINC OXIDE 14.5 g/100 mL
INACTIVE INGREDIENTS: PUERARIA MONTANA VAR. LOBATA ROOT 0.00015 mL/100 mL; TETRADECANE 5 mL/100 mL; WATER 53.8608 mL/100 mL; BENTONITE 1.5 mL/100 mL; CAPRYLYL GLYCOL 0.7 mL/100 mL; LEVOMENOL 0.3 mL/100 mL; CETOSTEARYL ALCOHOL 1.105 mL/100 mL; CHAMOMILE 0.00015 mL/100 mL; GLYCERIN 0.15845 mL/100 mL; SUNFLOWER OIL 6 mL/100 mL; HYDROGENATED JOJOBA OIL, RANDOMIZED 0.38 mL/100 mL; METHYL DIHYDROABIETATE 2 mL/100 mL; PROPANEDIOL 1 mL/100 mL; CARBOXYMETHYLCELLULOSE SODIUM, UNSPECIFIED FORM 0.09 mL/100 mL; BUTYLOCTYL SALICYLATE 5 mL/100 mL; CALENDULA OFFICINALIS FLOWER 0.00015 mL/100 mL; CAPRYLHYDROXAMIC ACID 0.15 mL/100 mL; MEDIUM-CHAIN TRIGLYCERIDES 3 mL/100 mL; SAFFLOWER OIL 3 mL/100 mL; COCO GLUCOSIDE 0.595 mL/100 mL; MICROCRYSTALLINE CELLULOSE 0.66 mL/100 mL; NASTURTIUM OFFICINALE FLOWERING TOP 0.00015 mL/100 mL; POLYHYDROXYSTEARIC ACID (2300 MW) 0.25 mL/100 mL; FILIPENDULA ULMARIA FLOWER 0.00015 mL/100 mL; TOCOPHEROL 0.75 mL/100 mL

8579 Babo SPF 30 Baby Skin Mineral Non-Aerosol Sunscreen Pump Spray, FF

SPF 30 Baby Skin Mineral Non-Aerosol Sunscreen Pump Spray, FF

This product is an OTC sunscreen manufactured according to the Sunscreen Final Rule. Active ingredient: Zinc Oxide

Active Ingredient

Zinc Oxide 14.5%; Purpose: Sunscreen

Uses

helps prevent sunburn • if used as directed with other sun protection measures (see Directions), decreases the risk of skin cancer and early skin aging caused by the sun

Purpose

Sunscreen

Warnings

For external use only.

Do not use

- on damaged or broken skin.

When using this product

Keep out of eye. Rinse with water to remove.

Stop use and ask doctor

if rash occurs

Keep out of reach of children. If swallowed, get medical help or contact a Poison Control center right away.

Directions

Apply liberally to exposed areas 15 minutes before sun exposure. Reapply at least every two hours, after 80 minutes of swimming or sweating, or immediately after towel-drying.

Sun Protection Measures• Spending time in the sun increases your risk of skin cancer and early skin aging. To decrease this risk, regularly use a sunscreen with a broad spectrum SPF of 15 or higher and other protection measures including: Limit time in the sun, especially from 10 a.m. – 2 p.m. and wear long-sleeve shirts, pants, hats, and sunglasses.

Children under 6 months; ask a doctor.

Inactive Ingredients

BENTONITE
BISABOLOL*
BUTYLOCTYL SALICYLATE
CALENDULA OFFICINALIS FLOWER EXTRACT*
CAPRYLHYDROXAMIC ACID
CAPRYLIC/CAPRIC TRIGLYCERIDE
CAPRYLYL GLYCOL
CARTHAMUS TINCTORIUS (SAFFLOWER) SEED OIL
CELLULOSE GUM
CETEARYL ALCOHOL
CHAMOMILLA RECUTITA (MATRICARIA) FLOWER EXTRACT*
COCO GLUCOSIDE
GLYCERIN*
HELIANTHUS ANNUUS (SUNFLOWER) SEED OIL*
JOJOBA ESTERS
METHYL DIHYDROABIETATE
MICROCRYSTALLINE CELLULOSE
NASTURTIUM OFFICINALE (WATERCRESS) FLOWER/LEAF EXTRACT*
POLYHYDROXYSTEARIC ACID
PROPANEDIOL
PUERARIA LOBATA (KUDZU) ROOT EXTRACT*
SPIRAEA ULMARIA (MEADOWSWEET) FLOWER EXTRACT*
TETRADECANE
TOCOPHEROL
WATER (AQUA)

Other information

Protect this product from excessive heat and direct sun. May stain some fabrics. You may report a serious adverse event to the phone number or address provided below.

Questions and comments

Call toll free 1-877-537-BABO Monday-Friday 9:00 am - 5:00 EST

PACKAGE LABEL

79265-8579-6 6 fl. oz. / 177 mL